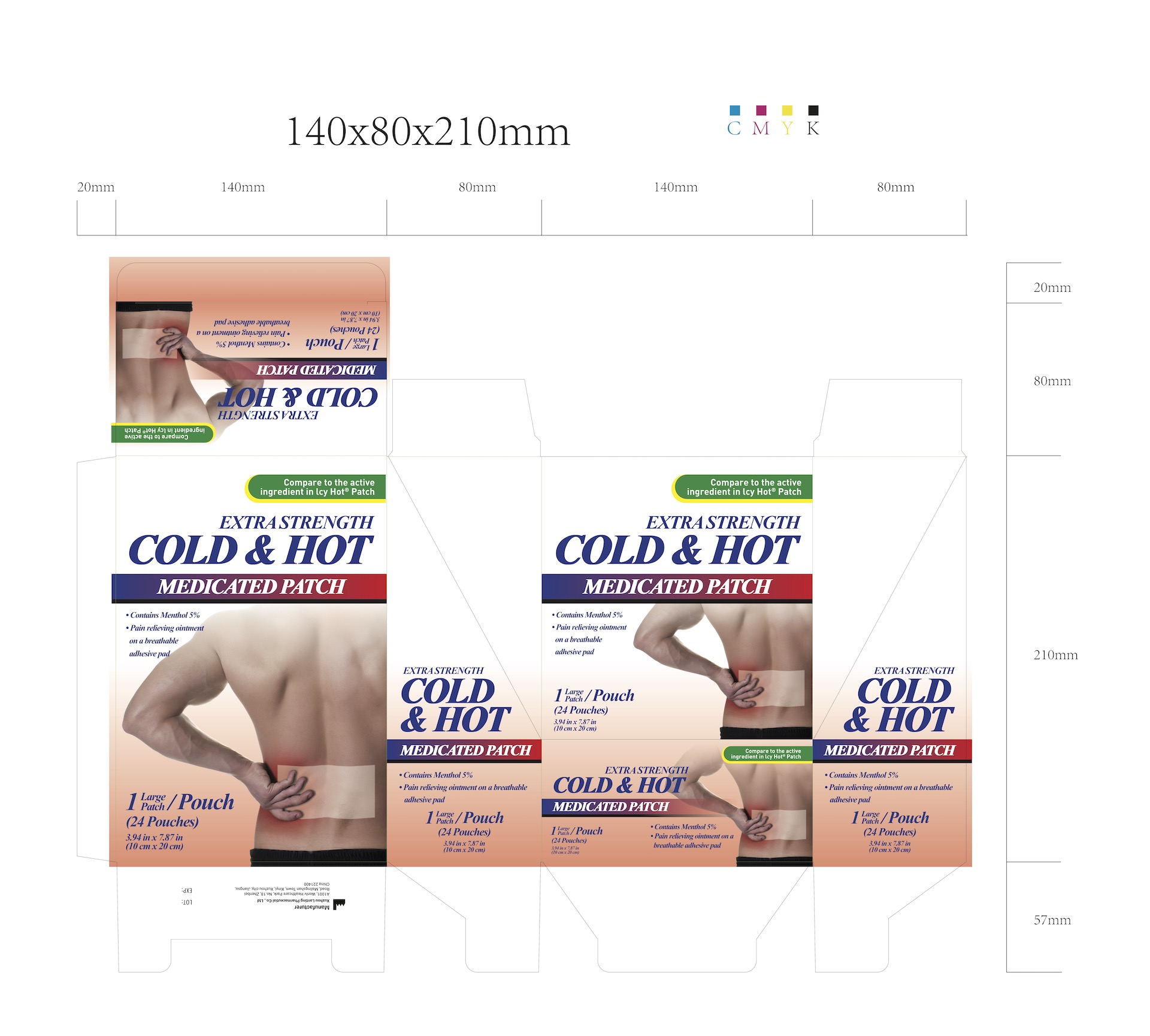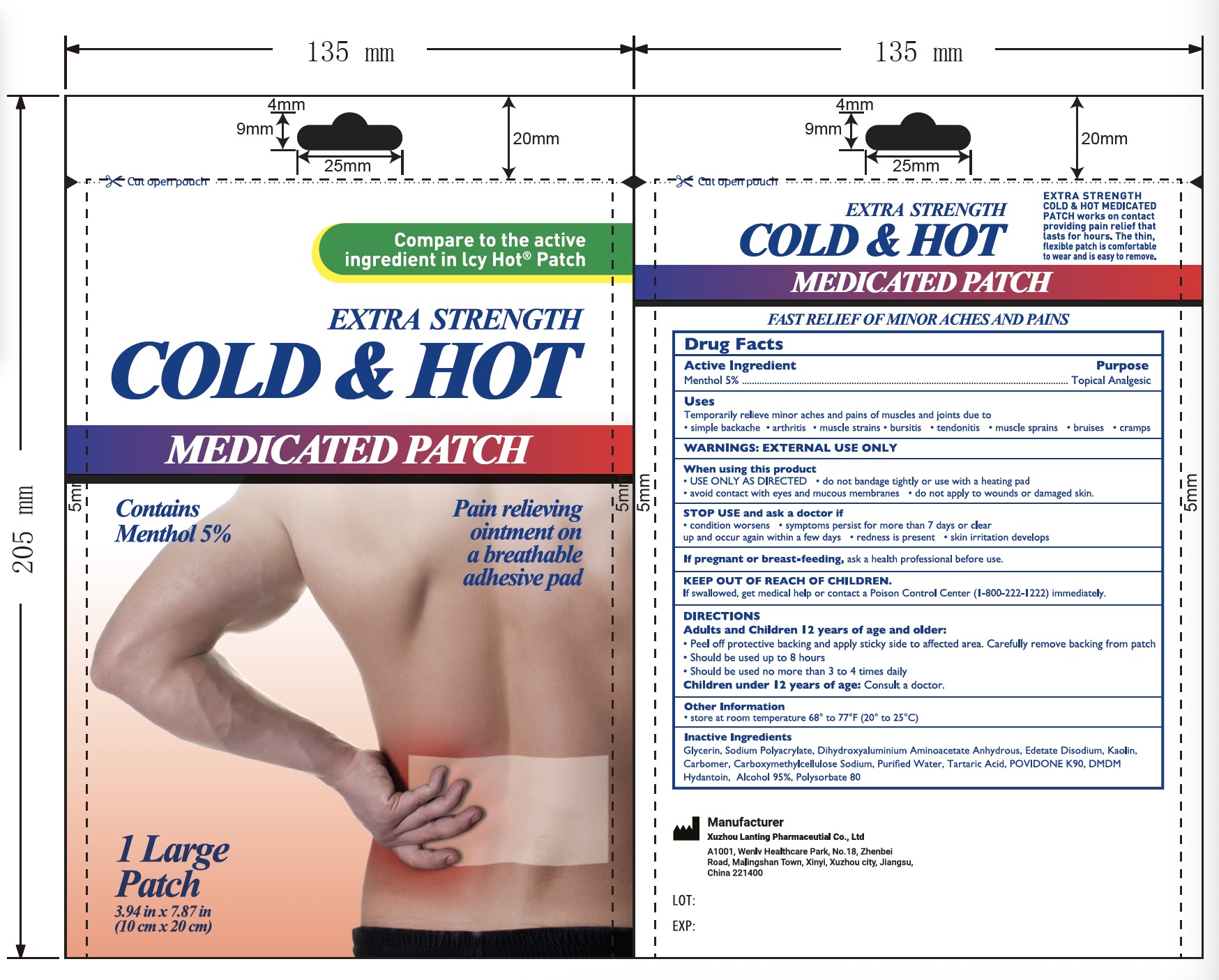 DRUG LABEL: 5% Menthol Pain Relief Patch
NDC: 85323-007 | Form: PATCH
Manufacturer: Xuzhou Lanting Pharmaceutical Co., Ltd
Category: otc | Type: HUMAN OTC DRUG LABEL
Date: 20250610

ACTIVE INGREDIENTS: MENTHOL 5 g/100 g
INACTIVE INGREDIENTS: WATER; POLYSORBATE 80; KAOLIN; SODIUM POLYACRYLATE (2500000 MW); CARBOMER 934; GLYCERIN; DMDM HYDANTOIN; CARBOXYMETHYLCELLULOSE SODIUM; EDETATE DISODIUM; DIHYDROXYALUMINUM AMINOACETATE ANHYDROUS; POVIDONE K90; TARTARIC ACID; ALCOHOL 95%

85323-007, 5% Menthol Pain Relief Patch

5% Menthol Pain Relief Patch, Package NDC Code 85323-007-01

Active Ingredient

Active Ingredient: Menthol 5%

Purpose

Purpose: Topical anesthetic

Warnings

For external use only.

- Do not use
- more than 1 patch at a time
- on wounds or damaged skin
- with a heating pad
- if you are allergic to any ingredients of this product

When using this product

- USE ONLY AS DIRECTED
- do not bandage tightly or use with a heating pad
- avoid contact with the eyes and mucous membranes
- do not apply to wounds or damaged skin.

Stop use and ask a doctor if

- condition worsens
- symptoms persist for more than 7 days or clear up and occur again within a few day
- redness is present
- skin irritation develops

If pregnant or breast-feeding, ask a health professional before use.

Keep out of reach of children. If swallowed, get medical help or contact a Poison Control Center (1-800-222-1222) immediately.

Inactive Ingredients

Glycerin, Sodium Polyacrylate, Dihydroxyaluminum Aminoacetate Anhydrous, Edetate Disodium, Kaolin, Carbomer, Carboxymethylcellulose Sodium, Purified Water, Tartaric Acid, Povidone K90, DMDM Hydantoin, Alcohol 95%, Polysorbate 80.

Keep out of reach of children.

If swallowed, get medical help or contact a Poison Control Center (1-800-222-1222) immediately.

Other information

- store at roo temperature 68 to 77℉ (20 to 25℃)

Directions

Adult and children 12 years of age and older:

- peel off protective backing and apply sticky side to affected area
- carefully remove backing from patch
- should be used to 8 hours
- ashould be used no more than 3 times a day
- Children under 12 years of age: consult a doctor

Uses

Temporarily relieve minor aches and pains of muscles and joints due to

- simple backache
- arthritis
- muscle strains
- bursitis
- tendonitis
- muscle sprains
- bruises
- cramps

INDICATIONS AND USAGE

Temporarily relieves minor pains associated with:

- arthritis
- simple backache
- muscle strains
- bursitis
- tendonitis
- sprains
- bruises
- cramps

Adult and Children 12 years of age and older:

- peel off protective backing and apply sticky side to affected area
- carefully remove backing from patch
- should be used to 8 hours
- ashould be used no more than 3 times a day
- Children under 12 years of age: consult a doctor